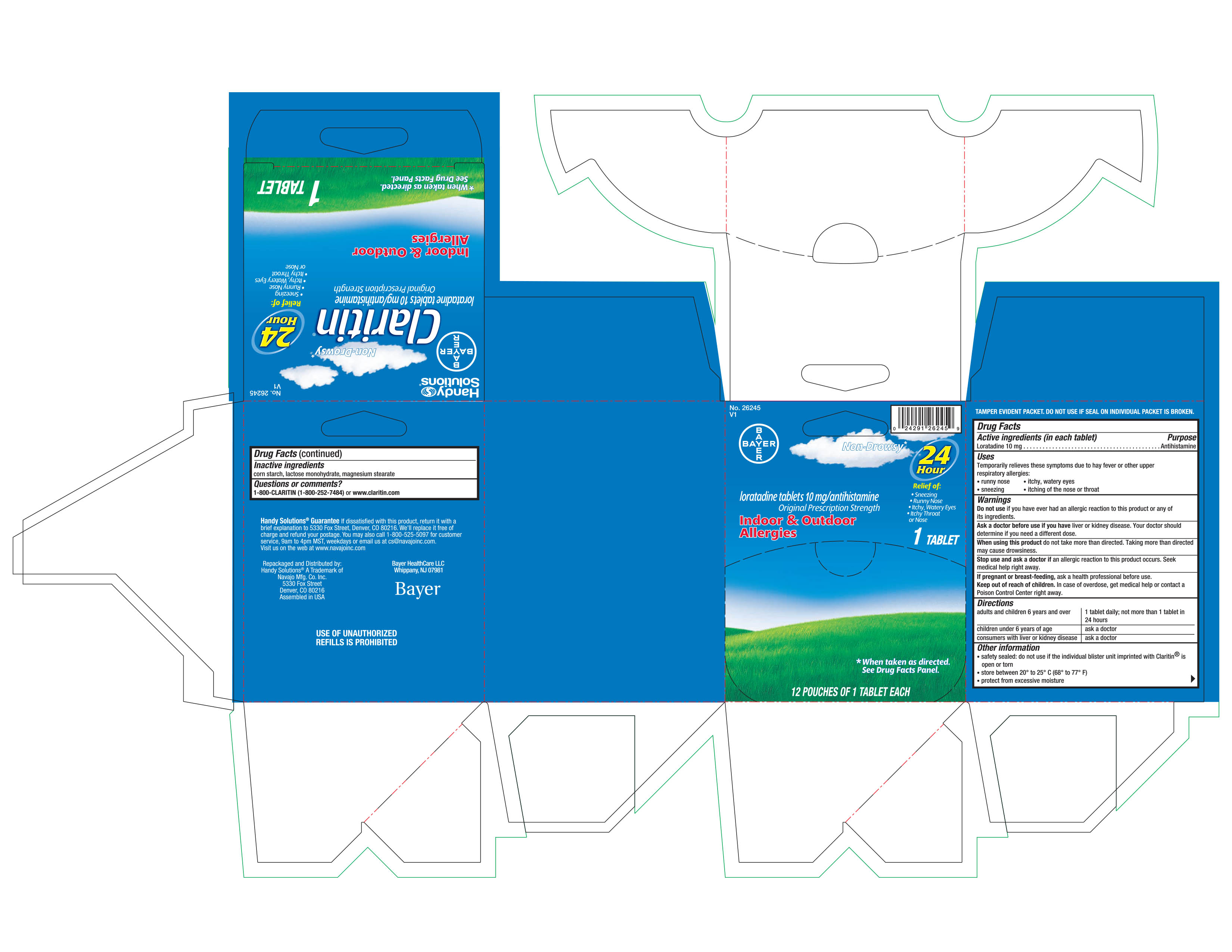 DRUG LABEL: Claritin
NDC: 67751-153 | Form: TABLET
Manufacturer: Navajo Manufacturing Company
Category: otc | Type: HUMAN OTC DRUG LABEL
Date: 20230301

ACTIVE INGREDIENTS: LORATADINE 10 mg/1 1
INACTIVE INGREDIENTS: STARCH, CORN; LACTOSE MONOHYDRATE; MAGNESIUM STEARATE

Claritin

Active ingredient (in each tablet)

Loratadine 10 mg

Purpose

Antihistamine

Uses

Temporarily relieves these symptoms due to hay fever or other upper respiratory allergies:

- runny nose
- itchy, watery eyes
- sneezing
- itching of the nose or throat

Warnings

Do not use if you have ever had an allergic reaction to this product or any of its ingredients.

Ask a doctor before use if you have liver or kidney disease. Your doctor should determine if you need a different dose.

When using this product do not take more than directed. Taking more than directed may cause drowsiness.

Stop use and ask a doctor if an allergic reaction to this product occurs. Seek medical help right away.

PREGNANCY OR BREAST FEEDING

If pregnant or breast-feeding, ask a health professional before use.

Keep out of reach of children. In case of overdose, get medical help or contact a Poison Control Center right away.

Directions

adults and children 6 years and over | 1 tablet daily; not more than 1 tablet in 24 hours
children under 6 years of age | ask a doctor
consumers with liver or kidney disease | ask a doctor

Other Information

- safety sealed: do not use if the individual blister unit imprinted with Claritin ® is open or torn
- store between 20° to 25°C (68° to 77°F)
- protect from excessive moisture

Inactive ingredients

corn starch, lactose monohydrate, magnesium stearate

Questions or Comments?

1-800-CLARITIN (1-800-252-7484) or www.claritin.com